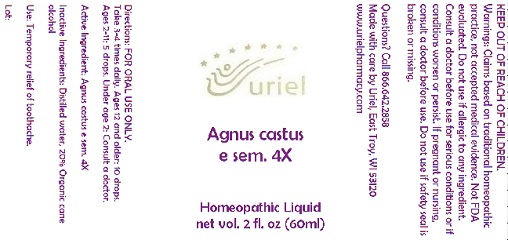 DRUG LABEL: Agnus castus e sem. 4
NDC: 48951-1024 | Form: LIQUID
Manufacturer: Uriel Pharmacy Inc.
Category: homeopathic | Type: HUMAN OTC DRUG LABEL
Date: 20191126

ACTIVE INGREDIENTS: ANGELICA ARCHANGELICA ROOT 1 [hp_X]/1 mL; ECHINACEA, UNSPECIFIED 1 [hp_X]/1 mL; LEVISTICUM OFFICINALE ROOT 2 [hp_X]/1 mL; ACMELLA OLERACEA WHOLE 2 [hp_X]/1 mL; CALENDULA OFFICINALIS FLOWERING TOP 3 [hp_X]/1 mL; CUPRIC ACETATE 3 [hp_X]/1 mL; INULA HELENIUM ROOT 6 [hp_X]/1 mL; PLANTAGO MAJOR LEAF 6 [hp_X]/1 mL; VERBASCUM DENSIFLORUM LEAF 6 [hp_X]/1 mL
INACTIVE INGREDIENTS: WATER; ALCOHOL

Agnus castus e sem. 4

INDICATIONS AND USAGE

Directions: FOR ORAL USE ONLY.

DOSAGE AND ADMINISTRATION

Take 3-4 times daily. Ages 12 and older: 10 drops. Ages 2-11: 5 drops. Under age 2: Consult a doctor.

Active Ingredient: Agnus castus e sem. 4X

Inactive Ingredients: Distilled water, 20% Organic cane alcohol

PURPOSE

Use: Temporary relief of toothache.

KEEP OUT OF REACH OF CHILDREN.

WARNINGS

Warnings: Claims based on traditional homeopathic practice, not accepted medical evidence. Not FDA evaluated. Do not use if allergic to any ingredient. Consult a doctor before use for serious conditions or if conditions worsen or persist. If pregnant or nursing, consult a doctor before use. Do not use if safety seal is broken or missing.

QUESTIONS

Questions? Call 866.642.2858 Made with care by Uriel, East Troy, WI 53120 www.urielpharmacy.com